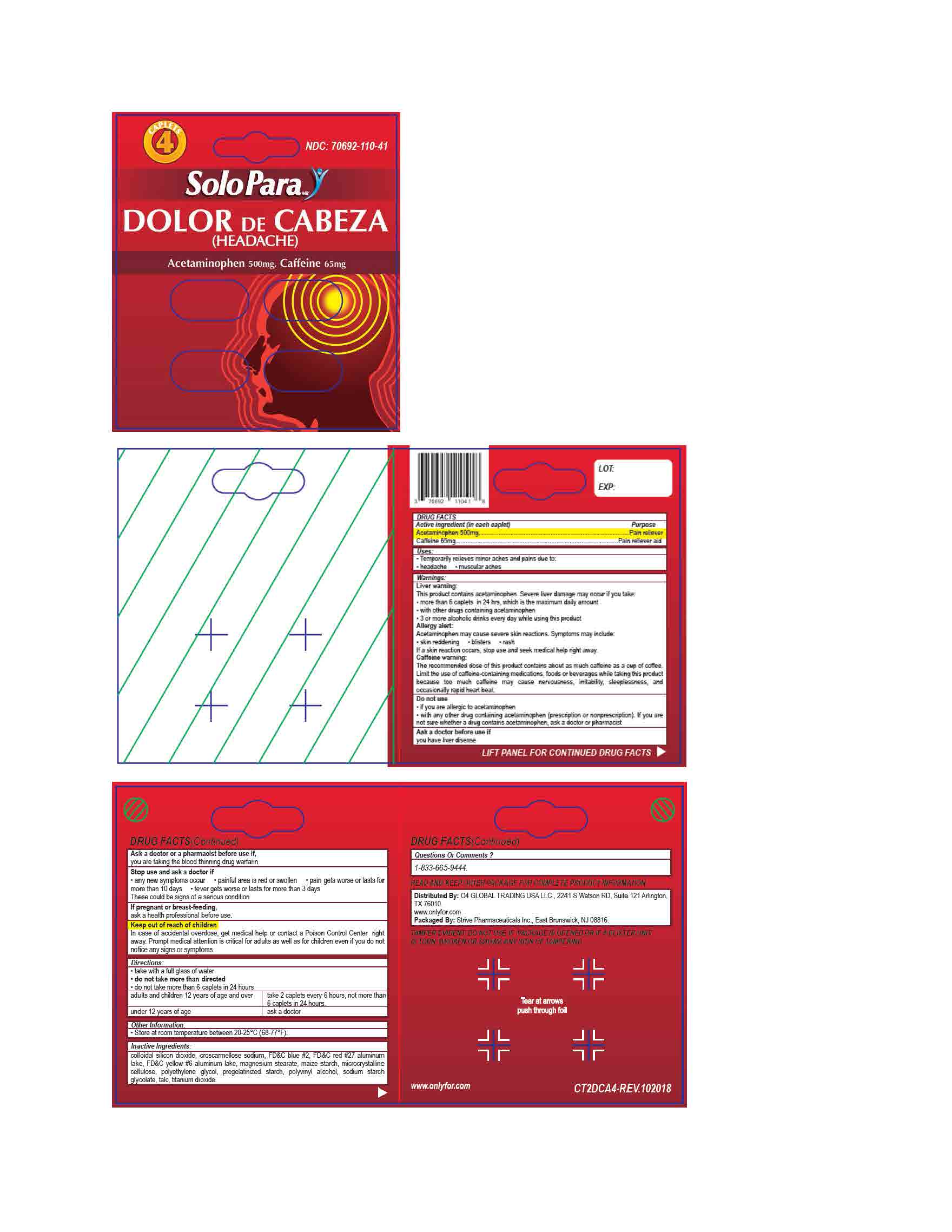 DRUG LABEL: Acetaminophen 500mg Caffeine 65mg
NDC: 70692-110 | Form: TABLET
Manufacturer: Strive Pharmaceuticals Inc
Category: otc | Type: HUMAN OTC DRUG LABEL
Date: 20201116

ACTIVE INGREDIENTS: ACETAMINOPHEN 500 mg/1 1; CAFFEINE 65 mg/1 1
INACTIVE INGREDIENTS: SILICON DIOXIDE; FD&C BLUE NO. 2; CROSCARMELLOSE SODIUM; MAGNESIUM STEARATE; STARCH, CORN; TALC; SODIUM STARCH GLYCOLATE TYPE A CORN; TITANIUM DIOXIDE; POLYVINYL ALCOHOL, UNSPECIFIED; FD&C YELLOW NO. 6; CELLULOSE, MICROCRYSTALLINE; POLYETHYLENE GLYCOL 400; D&C RED NO. 27

Headache - Dolor de Cabeza (Acetaminophen 500mg; Caffeine 65mg)

ACTIVE INGREDIENT

Acetaminophen 500mg; Caffeine 65mg

INACTIVE INGREDIENT

colloidal silicon dioxide, croscarmellose sodium, D&C red #27, FD&C blue #2, FD&C yellow #6, magnesium stearate, maize starch, microcrystalline cellulose, polyethylene glycol, pregalatinized starch, polyvinyl alcohol, sodium starch glycolate, talc, titanium dioxide

DOSAGE AND ADMINISTRATION

- take with a full glass of water
- do not take more than directed
- do not take more than 6 caplets in 24 hours

adults and children 12 years of age and over | take 2 caplets every 6 hours, not more than 6 caplets in 24 hours
children under 12 years of age | ask a doctor

INDICATIONS AND USAGE

*temporarily relieves minor aches and pains due to:

- headache
- muscular aches

WARNINGS

Liver warning:

This product contains acetaminophen. Severe liver damage may occur if you take:

- more than 6 caplets in 24 hours, which is the maimum daily amount
- with other drugs containing acetaminophen
- 3 or more alcoholic drinks every day while using this product

Allergy alert:

Acetaminophen may cause severe skin reactions. Symptoms may include:

- skin reddening
- blisters
- rash

if a skin reaction occurs, stop use and seek medical help right away

Caffeine warning:

The recommended dose of this product contains about as much caffeine as a cup of coffee. Limit the use of caffeine-containing medications, foods or beverages while takingthis product because too much caffeine may cause nervousness, irritability, sleeplessness, and occassionally rapis heart beat.

Do not use

- if you are allergic to acetaminophen
- with any other drug containing acetaminophen (prescription or non prescription). If you are not sure whether a drug contains acetaminophen, ask a doctor or pharmacist

Ask a doctor before use if you have

- liver disease

Ask a doctor or a pharmacist before use if

you are taking the blood thinning drug warfarin

Stop use and ask a doctor if

- pain gets worse or lasts more than 10 days
- new symptoms occur
- painful area is red or swollen

These could be signs of a serious comdition

If pregnant or breast-feeding,

ask a health professional before use

Keep out of reach of children

Overdose warning: In case of accidental overdose, get medical help or contact a Poison Control Center right away. Prompt medical attention is critical for adults as well as for children even if you do not notice any signs or symptoms.

Keep out of reach of children

Overdose Warning: In case of accidental overdose, get medical help or contact a Poison Control Center right away. Prompt medical attention is critical for adults as well as for children even if you do not notice any signs or symptoms.

PURPOSE

Pain reliever ; Pain reliever aid

OTHER SAFETY INFORMATION

- store at room temperature between 20ºC - 25ºC (68ºF - 77ºF)